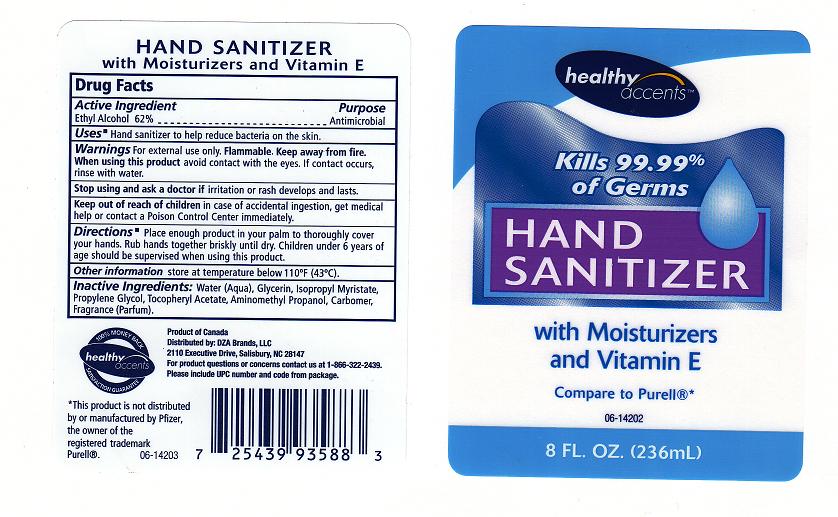 DRUG LABEL: HAND SANITIZER
NDC: 55316-225 | Form: GEL
Manufacturer: DZA BRANDS
Category: otc | Type: HUMAN OTC DRUG LABEL
Date: 20111013

ACTIVE INGREDIENTS: ALCOHOL 62 mL/100 mL
INACTIVE INGREDIENTS: WATER; GLYCERIN; ISOPROPYL MYRISTATE; PROPYLENE GLYCOL; .ALPHA.-TOCOPHEROL ACETATE, D-; AMINOMETHYLPROPANOL; CARBOMER 934

Drug Facts

ACTIVE INGREDIENT

ETHYL ALCOHOL 62%

PURPOSE

ANTIMICROBIAL

USES

HAND SANITIZER TO HELP REDUCE BACTERIA ON THE SKIN.

WARNINGS

FOR EXTERNAL USE ONLY. KEEP AWAY FROM FIRE.

WHEN USING THIS PRODUCT

AVOID CONTACT WITH EYES. IF CONTACT OCCURS, RINSE WITH WATER.

STOP USING THIS PRODUCT AND ASK A DOCTOR IF

IRRITATION OR RASH DEVELOPS AND LASTS.

KEEP OUT OF REACH OF CHILDREN

IN CASE OF ACCIDENTAL INGESTION, GET MEDICAL HELP OR CONTACT A POISON CONTROL CENTER IMMEDIATELY.

DIRECTIONS

PLACE ENOUGH PRODUCT IN YOUR PALM TO THOROUGHLY COVER YOUR HANDS. RUB HANDS TOGETHER BRISKLY UNTIL DRY. CHILDREN UNDER 6 YEARS OF AGE SHOULD BE SUPERVISED WHEN USING THIS PRODUCT.

OTHER INFORMATION

STORE AT TEMPERATURE BELOW 110^0C (43^0C)

INACTIVE INGREDIENTS

WATER, GLYCERIN, ISOPROPYL MYRISTATE, PROPYLENE GLYCOL, TOCOPHERYL ACETATE, AMINOMETHYL PROPANOL, CARBOMER, FRAGRANCE.